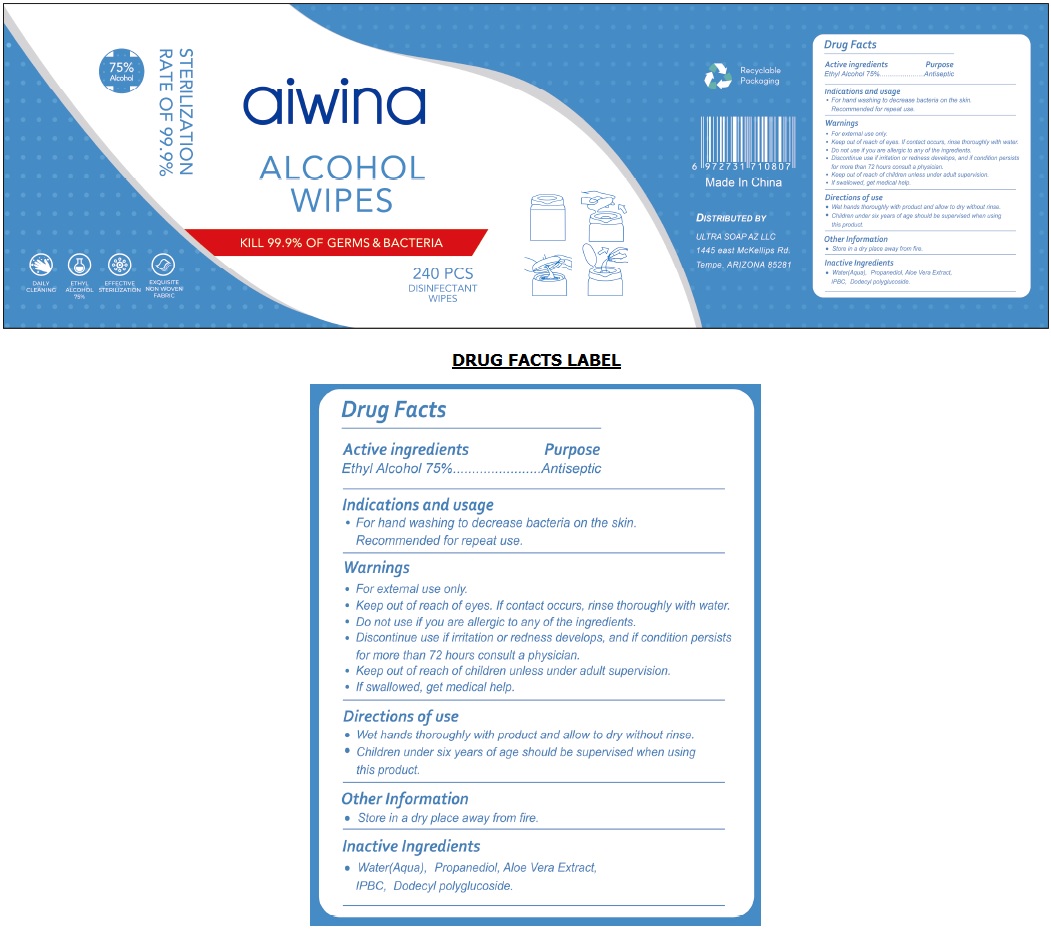 DRUG LABEL: aiwina ALCOHOL WIPES
NDC: 79891-111 | Form: CLOTH
Manufacturer: DOBOLV (QUANZHOU) PAPER CO., LTD
Category: otc | Type: HUMAN OTC DRUG LABEL
Date: 20201123

ACTIVE INGREDIENTS: ALCOHOL 75 mL/100 mL
INACTIVE INGREDIENTS: WATER; PROPANEDIOL; ALOE VERA LEAF; IODOPROPYNYL BUTYLCARBAMATE; LAURYL GLUCOSIDE

aiwina ALCOHOL WIPES

Active ingredients

Ethyl Alcohol 75%

Purpose

Antiseptic

Indications and usage

• For hand washing to decrease bacteria on the skin.

Recommended for repeat use.

Warnings

• For external use only.

• Keep out of reach of eyes. If contact occurs, rinse thoroughly with water.

• Do not use if you are allergic to any of the ingredients.

• Discontinue use if irritation or redness develops, and if condition persists for more than 72 hours consult a physician.

• Keep out of reach of children unless under adult supervision.

• If swallowed, get medical help.

Directions of use

• Wet hands thoroughly with product and allow to dry without rinse.

• Children under six years of age should be supervised when using this product.

Other Information

• Store in a dry place away from fire.

Inactive Ingredients

• Water(Aqua), Propanediol, Aloe Vera Extract, IPBC, Dodecyl polyglucoside.

KILL 99.9% OF GERMS & BACTERIA

75% Alcohol

STERILIZATION RATE OF 99.9%

DAILY CLEANING

EFFECTIVE STERILIZATION

EXQUISITE NON WOVEN FABRIC

Made In China

DISTRIBUTED BY

ULTRA SOAP AZ LLC

1445 east McKellips Rd.

Tempe, ARIZONA 85281